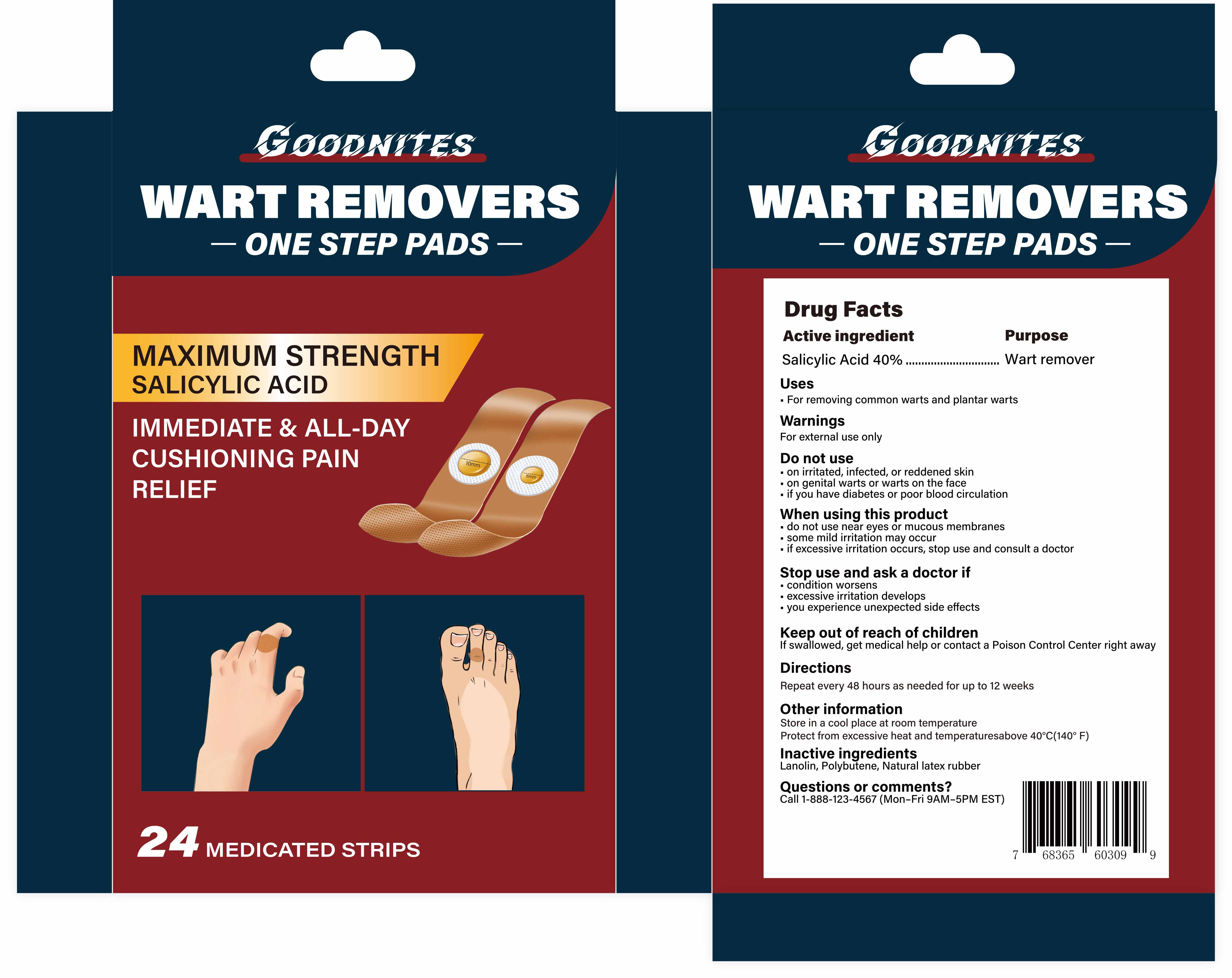 DRUG LABEL: Goodnites Wart Remover Bandaid
NDC: 85578-004 | Form: PATCH
Manufacturer: Zhengzhou Hangrui Network Technology Co., Ltd.
Category: otc | Type: HUMAN OTC DRUG LABEL
Date: 20250811

ACTIVE INGREDIENTS: SALICYLIC ACID 5 mg/1 1
INACTIVE INGREDIENTS: LANOLIN; POLYBUTENE (1400 MW); NATURAL LATEX RUBBER

85578-004 Goodnites Wart Remover Bandaid

ACTIVE INGREDIENT

Salicylic Acid 40%

PURPOSE

Wart remover

INDICATIONS AND USAGE

.For removing common warts and plantar warts

WARNINGS

For external use only

DO NOT USE

.on irritated,infected, or reddened skin

on genital warts or warts on the face

if you have diabetes or poor blood circulation

do not use near eyes or mucous membranes
some mild irritation may occur
if excessive irritation occurs, stop use and consult a doctor

STOP USE

condition worsens
excessive irritation develops
you experience unexpected side effects

KEEP OUT OF REACH OF CHILDREN

If swallowed, get medical help or contact a Poison Control Center right away

DOSAGE AND ADMINISTRATION

Repeat every 48 hours as needed for up to 12 weeks

INACTIVE INGREDIENT

LANOLIN
POLYBUTENE (1400 MW)
NATURAL LATEX RUBBER